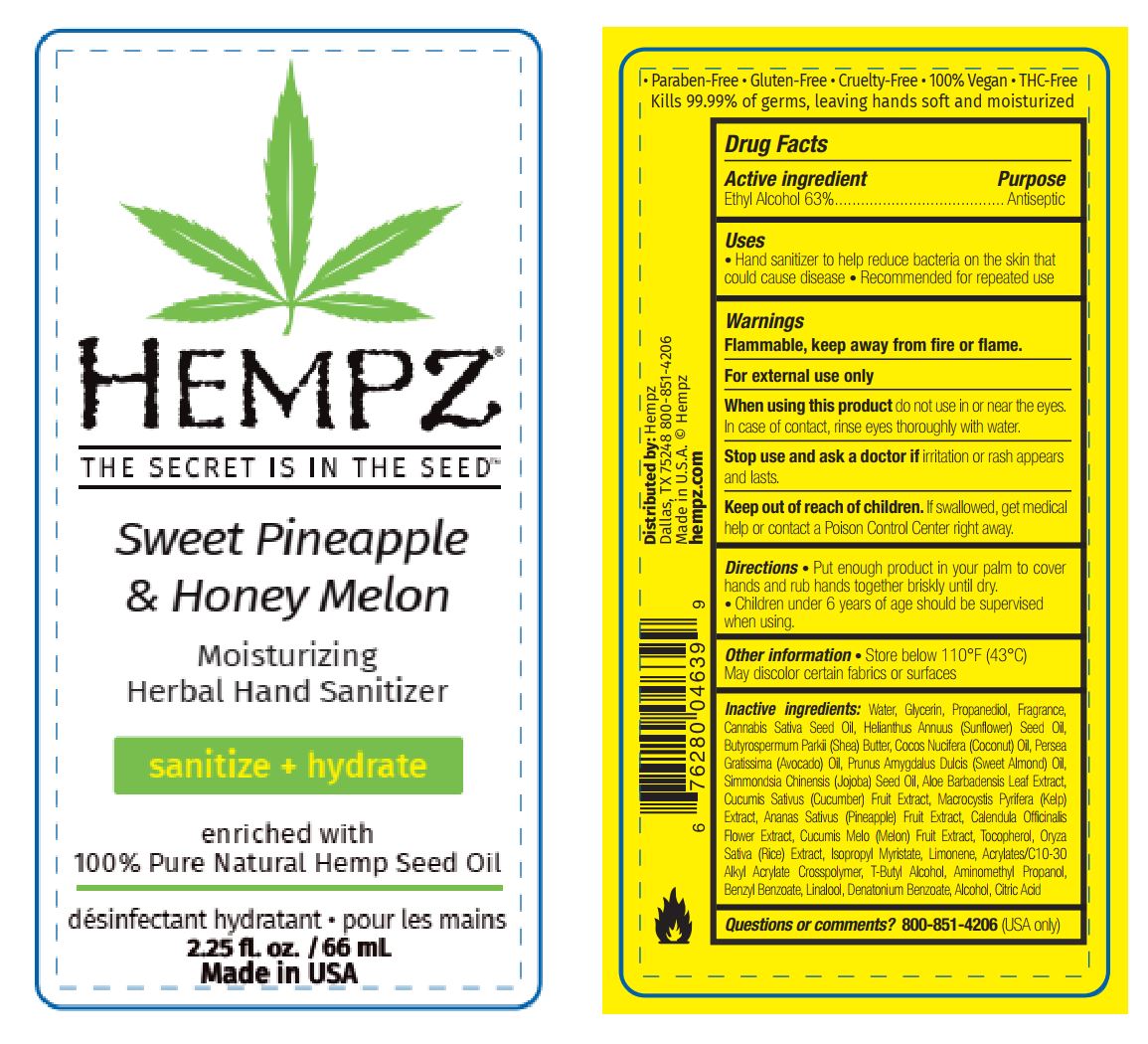 DRUG LABEL: HEMPZ SWEET PINEAPPLE HONEY MELON MOISTURIZING HERBAL HAND SANITIZER
NDC: 84853-0003 | Form: GEL
Manufacturer: PBIGROUP, LLC
Category: otc | Type: HUMAN OTC DRUG LABEL
Date: 20241023

ACTIVE INGREDIENTS: ALCOHOL 41.58 g/66 mL
INACTIVE INGREDIENTS: CALENDULA OFFICINALIS FLOWER; ACRYLATES/C10-30 ALKYL ACRYLATE CROSSPOLYMER (60000 MPA.S AT 0.5%); AMINOMETHYLPROPANOL; DENATONIUM BENZOATE ANHYDROUS; MUSKMELON; RICE GERM; COCONUT OIL; LINALOOL, (+/-)-; TERT-BUTYL ALCOHOL; PINEAPPLE; TOCOPHEROL; CITRIC ACID MONOHYDRATE; WATER; GLYCERIN; PROPANEDIOL; CANNABIS SATIVA SEED OIL; SUNFLOWER OIL; SHEA BUTTER; AVOCADO OIL; ALMOND OIL; JOJOBA OIL; ALOE VERA LEAF; CUCUMBER; BENZYL BENZOATE; MACROCYSTIS PYRIFERA; LIMONENE, (+)-

HEMPZ SWEET PINEAPPLE & HONEY MELON MOISTURIZING HERBAL HAND SANITIZER

Active ingredient

Ethyl Alcohol 63%

Purpose

Antiseptic

Uses

- Hand sanitizer to help reduce bacteria on the skin that could cause disease
- Recommended for repeated use

Warnings

Flammable, keep away from fire or flame.

For external use only

When using this product

Do not use in or near the eyes. In case of contact, rinse eyes thoroughly with water.

Stop use and ask a doctor if

Irritation or rash appears and lasts.

Keep out of reach of children

If swallowed, get medical help or contact a Poison Control Center right away.

Directions

Put enough product in your palm to cover hands and rub hands together briskly until dry. Children under 6 years of age should be supervised when using.

Other information

Store below 110°F (43°C). May discolor certain fabrics or surfaces.

Inactive ingredients

Water, Glycerin, Propanediol, Fragrance, Cannabis Sativa Seed Oil, Helianthus Annuus (Sunflower) Seed Oil, Butyrospermum Parkii (Shea) Butter, Cocos Nucifera (Coconut) Oil, Persea Gratissima (Avocado) Oil, Prunus Amygdalus Dulcis (Sweet Almond) Oil, Simmondsia Chinensis (Jojoba) Seed Oil, Aloe Barbadensis Leaf Extract, Cucumis Sativus (Cucumber) Fruit Extract, Macrocystis Pyrifera (Kelp) Extract, Ananas Sativus (Pineapple) Fruit Extract, Calendula Officinalis Flower Extract, Cucumis Melo (Melon) Fruit Extract, Tocopherol, Oryza Sativa (Rice) Extract, Isopropyl Myristate, Limonene, Acrylates/C10-30 Alkyl Acrylate Crosspolymer, T-Butyl Alcohol, Aminomethyl Propanol, Benzyl Benzoate, Linalool, Denatonium Benzoate, Alcohol, Citric Acid.

Questions or comments?

800-851-4206 (USA only)

SPL Unclassified

• Paraben-Free • Gluten-Free • Cruelty-Free • 100% Vegan • THC-Free
Kills 99.99% of germs, leaving hands soft and moisturized

Distributed by:Hempz

Dallas, TX 75248 800-851-4206

Made in U.S.A. Hempz

hempz.com